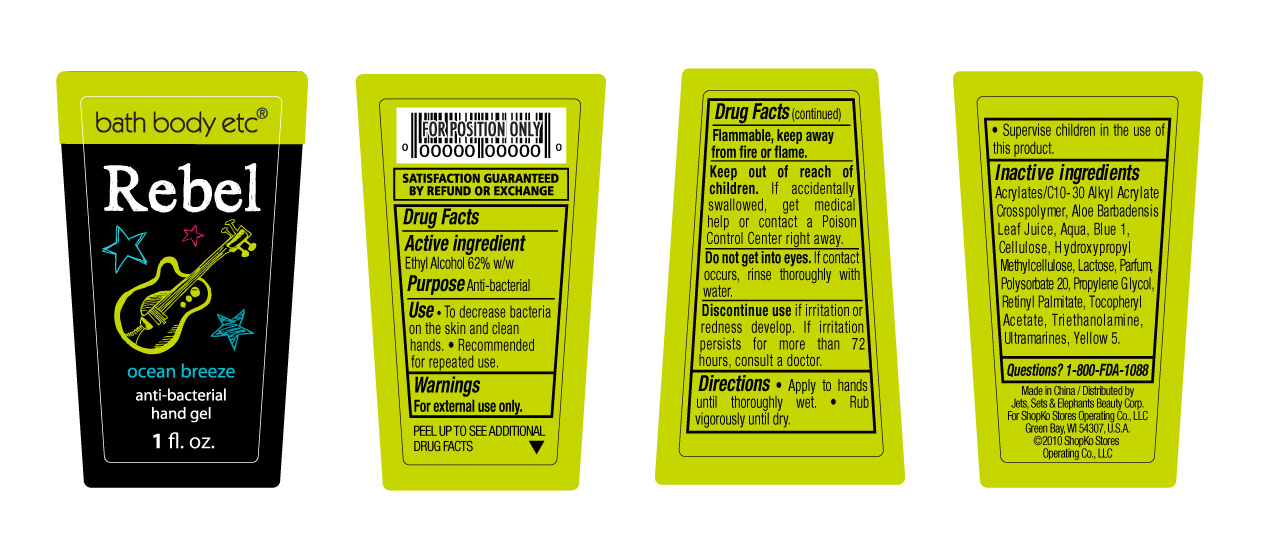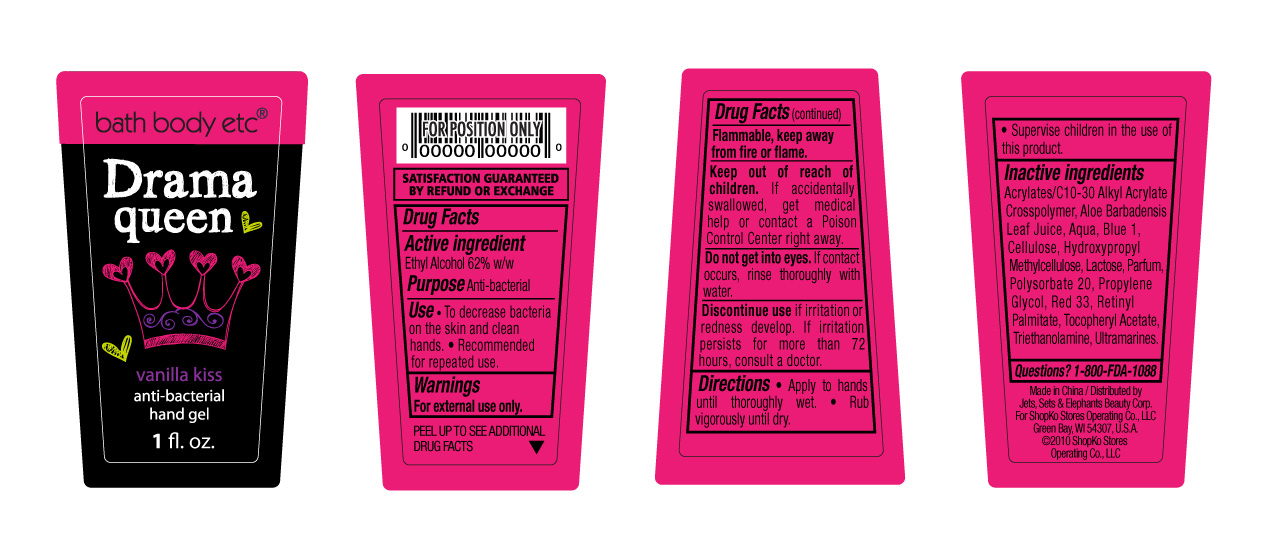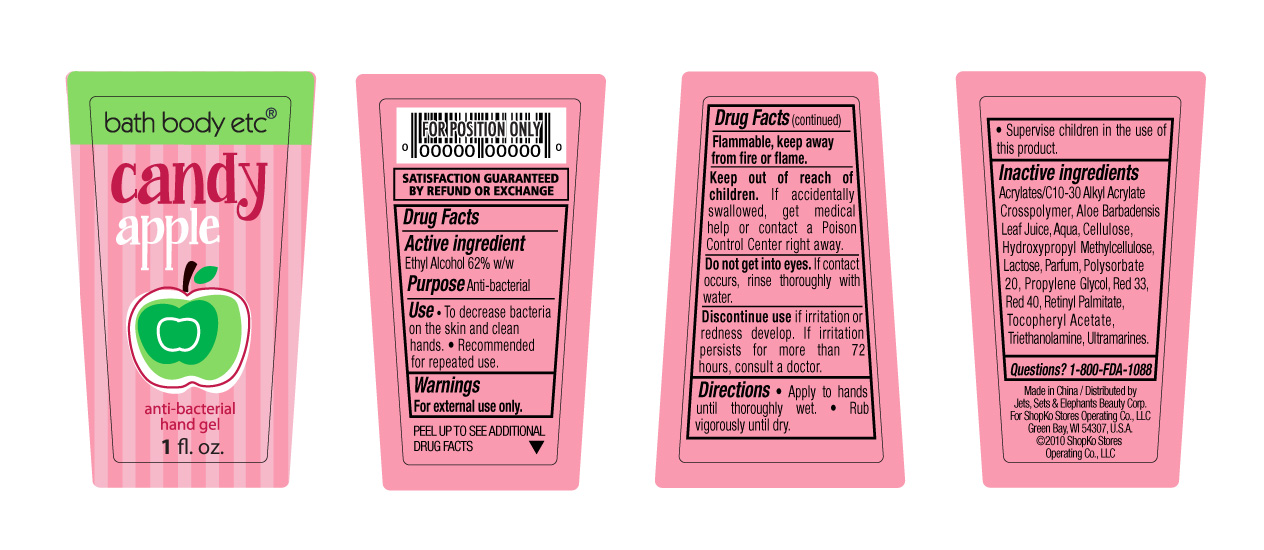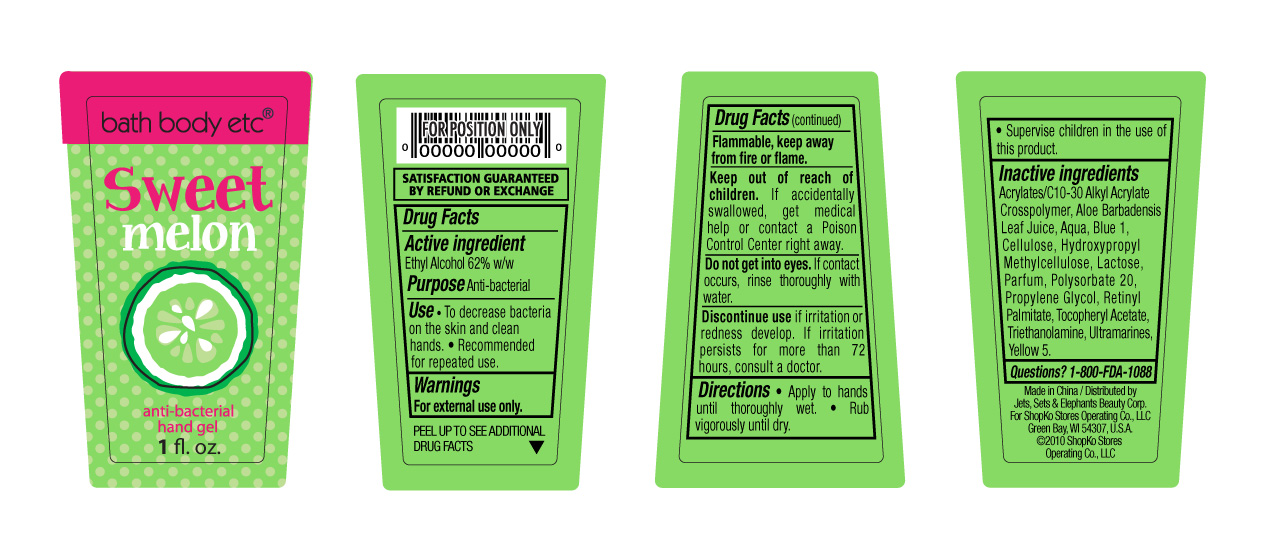 DRUG LABEL: Shopko Antibacterial Hand Sanitizer
NDC: 50988-280 | Form: GEL
Manufacturer: Jets, Sets, & Elephants Beauty Corp.
Category: otc | Type: HUMAN OTC DRUG LABEL
Date: 20120321

ACTIVE INGREDIENTS: ALCOHOL 0.62 mL/1 mL
INACTIVE INGREDIENTS: WATER; PROPYLENE GLYCOL; ALOE VERA LEAF; POLYSORBATE 20; TROLAMINE; VITAMIN A PALMITATE; LACTOSE; HYPROMELLOSE 2208 (100 MPA.S); .ALPHA.-TOCOPHEROL ACETATE; ULTRAMARINE BLUE; FD&C RED NO. 40; FD&C BLUE NO. 1; FD&C YELLOW NO. 5

bath body etc® anti-bacterial hand gel - Rebel ocean breeze, Drama queen vanilla kiss, Candy apple, and Sweet melon

ACTIVE INGREDIENT

Ethyl Alcohol 62% w/w

PURPOSE

Anti-bacterial

USE

- To decrease bacteria on the skin and clean hands.
- Recommended for repeated use.

WARNINGS

For external use only. Flammable, keep away from fire or flame.

Keep out of reach of children.

If accidentally swallowed, get medical help or contact a Poison Control Center right away.

Do not get into eyes.

If contact occurs, rinse thoroughly with water.

Discontinue use

if irritation or redness develop. If irritation persists for more than 72 hours, consult a doctor.

DIRECTIONS

- Apply to hands until thoroughly wet.
- Rub vigorously until dry.
- Supervise children in the use of this product.

Inactive Ingredients

Rebel ocean breeze

Acrylates/C10-30 Alkyl Acrylate Crosspolymer, Aloe Barbadensis Leaf Juice, Aqua, Blue 1, Cellulose, Hydroxypropyl Methylcellulose, Lactose, Parfum, Polysorbate 20, Propylene Glycol, Retinyl Palmitate, Tocopheryl Acetate, Triethanolamine, Ultramarines, Red 40, Yellow 5

Drama queen vanilla kiss

Acrylates/C10-30 Alkyl Acrylate Crosspolymer, Aloe Barbadensis Leaf Juice, Aqua, Blue 1, Cellulose, Hydroxypropyl Methylcellulose, Lactose, Parfum, Polysorbate 20, Propylene Glycol, Red 33, Retinyl Palmitate, Tocopheryl Acetate, Triethanolamine, Ultramarines

Candy apple

Acrylates/C10-30 Alkyl Acrylate Crosspolymer, Aloe Barbadensis Leaf Juice, Aqua, Cellulose, Hydroxypropyl Methylcellulose, Lactose, Parfum, Polysorbate 20, Propylene Glycol, Red 33, Red 40, Retinyl Palmitate, Tocopheryl Acetate, Triethanolamine, Ultramarines

Sweet melon

Acrylates/C10-30 Alkyl Acrylate Crosspolymer, Aloe Barbadensis Leaf Juice, Aqua, Blue 1, Cellulose, Hydroxypropyl Methylcellulose, Lactose, Parfum, Polysorbate 20, Propylene Glycol, Retinyl Palmitate, Tocopheryl Acetate, Triethanolamine, Ultramarines, Yellow 5

QUESTIONS?

1-800-FDA-1088

Made in China

Distributed by Jets, Sets & Elephants Beauty Corp.

For ShopKo Stores Operating Co., LLC

Green Bay, WI 54307, U.S.A

©2010 ShopKo Stores Operating Co., LLC

PACKAGE/LABEL PRINCIPAL DISPLAY PANEL - BOTTLE LABEL

bath body etc®

Rebel ocean breeze

anti-bacterial

hand gel

1 fl. oz.

Rebel ocean breeze Bottle Label

PACKAGE/LABEL PRINCIPAL DISPLAY PANEL - BOTTLE LABEL

bath body etc®

Drama queen vanilla kiss

anti-bacterial

hand gel

1 fl. oz.

Drama queen vanilla kiss Bottle Label

PACKAGE/LABEL PRINCIPAL DISPLAY PANEL - BOTTLE LABEL

bath body etc®

Candy apple

anti-bacterial

hand gel

1 fl. oz.

Candy apple Bottle Label

PACKAGE/LABEL PRINCIPAL DISPLAY PANEL - BOTTLE LABEL

bath body etc®

Sweet melon

anti-bacterial

hand gel

1 fl. oz.

Sweet melon Bottle Label